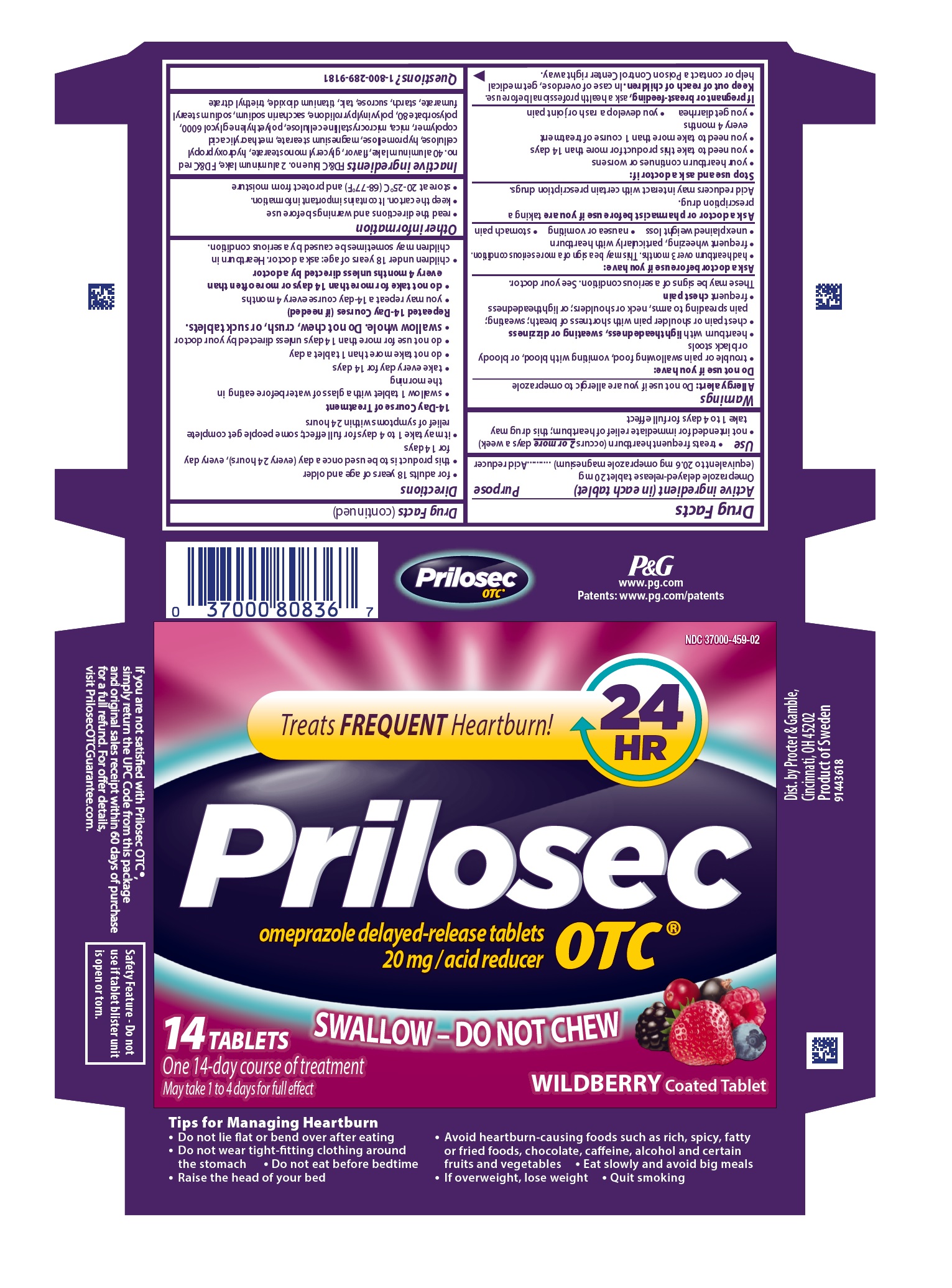 DRUG LABEL: Prilosec OTC
NDC: 37000-459 | Form: TABLET, DELAYED RELEASE
Manufacturer: The Procter & Gamble Manufacturing Company
Category: otc | Type: HUMAN OTC DRUG LABEL
Date: 20251001

ACTIVE INGREDIENTS: OMEPRAZOLE MAGNESIUM 20 mg/1 1
INACTIVE INGREDIENTS: STARCH, RICE; POVIDONE K60; TRIETHYL CITRATE; FD&C BLUE NO. 2--ALUMINUM LAKE; FD&C RED NO. 40; METHACRYLIC ACID - METHYL METHACRYLATE COPOLYMER (1:1); GLYCERYL MONOSTEARATE; HYDROXYPROPYL CELLULOSE (1600000 WAMW); HYPROMELLOSES; MAGNESIUM STEARATE; MICA; CELLULOSE, MICROCRYSTALLINE; POLYETHYLENE GLYCOL 6000; POLYSORBATE 80; SACCHARIN SODIUM; SODIUM STEARYL FUMARATE; SUCROSE; TALC; TITANIUM DIOXIDE

Prilosec OTC®
WILDBERRY

Drug Facts

Active ingredient (in each tablet)

Omeprazole delayed-release tablet 20 mg (equivalent to 20.6 mg omeprazole magnesium)

Purpose

Acid reducer

Use

- treats frequent heartburn (occurs 2 or moredays a week)
- not intended for immediate relief of heartburn; this drug may take 1 to 4 days for full effect

Warnings

Allergy alert:
• Do not use if you are allergic to omeprazole.
• Omeprazole may cause severe skin reactions. Symptoms may include:
• skin reddening • blisters • rash
If an allergic reaction occurs, stop use and seek medical help right away.

Do not use if you have:

- trouble or pain swallowing food, vomiting with blood, or bloody or black stools
- heartburn with lightheadedness, sweating or dizziness
- chest pain or shoulderpain with shortness of breath; sweating; pain spreading to arms, neck, or shoulders; or lightheadedness
- frequent chest pain

These may be signs of a serious condition. See your doctor.

Ask a doctor before use if you have:

- had heartburn over 3 months. This may be a sign of a more serious condition.
- frequent wheezing, particularly with heartburn
- unexplained weight loss
- nausea or vomiting
- stomach pain

Ask a doctor or pharmacist before use if you are

taking a prescription drug.
Acid reducers may interact with certain prescription drugs.

Stop use and ask a doctor if:

• your heartburn continues or worsens
• you need to take this product for more than 14 days
• you need to take more than 1 course of treatment every 4 months
• you get diarrhea

• you develop a rash or joint pain

If pregnant or breast-feeding,

ask a health professional before use.

Keep out of reach of children.

OVERDOSAGE

In case of overdose, get medical help or contact a Poison Control Center right away.

Directions

- for adults 18 years of age and older
- this product is to be used once a day (every 24 hours), every day for 14 days
- it may take 1 to 4 days for full effect; some people get complete relief of symptoms within 24 hours
  14-Day Course of Treatment
  - swallow 1 tablet with a glass of water before eating in the morning
  - take every day for 14 days
  - do not take more than 1 tablet a day
  - do not use for more than 14 days unless directed by your doctor
  - swallow whole. Do not chew, crush, or suck tablets.
  Repeated 14-Day Courses (if needed)
  - you may repeat a 14-day course every 4 months
  - do not take for more than 14 days or more often than every 4 months unless directed by a doctor
- children under 18 years of age: ask a doctor. Heartburn in children may sometimes be caused by a serious condition.

Other information

- read the directions and warnings before use
- keep the carton. It contains important information.
- store at 20-25°C (68-77°F) and protect from moisture

Inactive ingredients

FD&C blue no. 2 aluminum lake, FD&C red no. 40 aluminum lake, flavor, glyceryl monostearate, hydroxypropyl cellulose, hypromellose, magnesium stearate, methacrylic acid copolymer, mica, microcrystalline cellulose, polyethylene glycol 6000, polysorbate 80, polyvinylpyrrolidone, saccharin sodium, sodium stearyl fumarate, starch, sucrose, talc, titanium dioxide, triethyl citrate

Questions?

1-800-289-9181

Safety Feature - Do not use if tablet blister unit is open or torn.

Dist. by Procter & Gamble,
Cincinnati, OH 45202

Product of Sweden

PRINCIPAL DISPLAY PANEL - 14 Tablet Carton

See current Drug Facts NDC 37000-459-02

Treats FREQUENT Heartburn! 24 HR

Prilosec OTC ®

omeprazole delayed-release tablets

20 mg / acid reducer

SWALLOW - DO NOT CHEW

14 TABLETS
One 14-day course of treatment

May take 1 to 4 days for full effect
WILDBERRY Coated Tablet